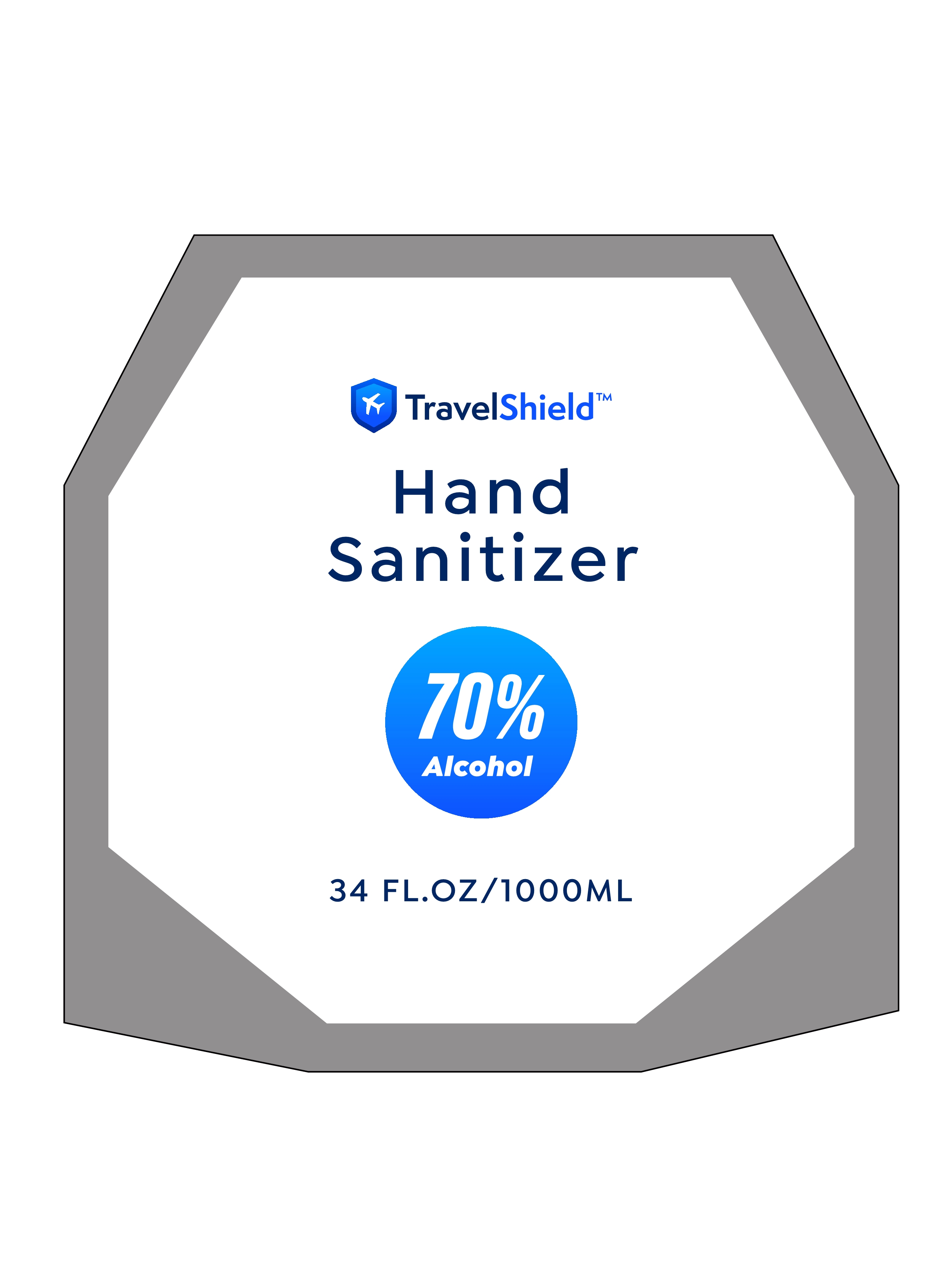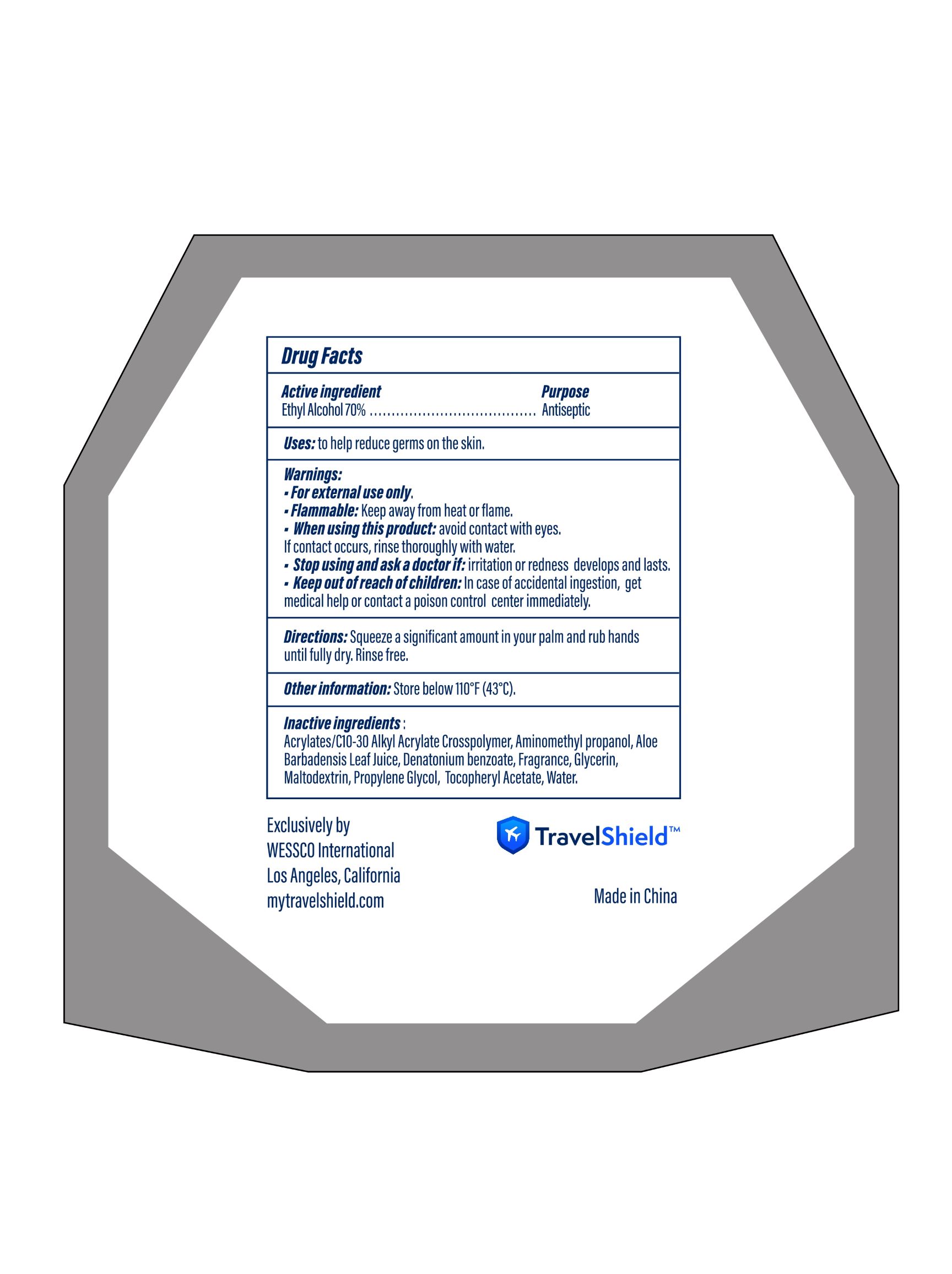 DRUG LABEL: Hand Sanitizer
NDC: 42509-036 | Form: GEL
Manufacturer: WESSCO International
Category: otc | Type: HUMAN OTC DRUG LABEL
Date: 20210219

ACTIVE INGREDIENTS: ALCOHOL 70 mL/100 mL
INACTIVE INGREDIENTS: CARBOMER INTERPOLYMER TYPE A (55000 CPS); GLYCERIN; PROPYLENE GLYCOL; WATER; FRAGRANCE LAVENDER & CHIA F-153480; DENATONIUM BENZOATE; .ALPHA.-TOCOPHEROL ACETATE; MALTODEXTRIN; ALOE VERA LEAF; AMINOMETHYLPROPANOL

WESSCO International
Hand Sanitizer 1000ml

Active Ingredient(s)

Ethyl Alcohol 70% v/v.

Purpose

Antiseptic, Hand Sanitizer

Use

Hand Sanitizer to help reduce germs on the skin.

Warnings

- For external use only.
- Flammable: Keep away from heat or flame.

Do not use

- in children less than 2 months of age
- on open skin wounds

When using this product: avoid contact with eyes. lf contact occurs, rinse thoroughly with water.

STOP USE

Stop using and ask a doctor if irritation or redness develops and lasts.

Keep out of reach of children: ln case of accidental ingestion, get medical help or contact a poison control center immediately.

Directions

- Squeeze a significant amount in your palm and rub hands until fully dry.
- Rinse free.

Other information

- Store below 110 °F（43° C).

Inactive ingredients

Acrylates/C10-30 Alkyl Acrylate Crosspolymer, Aminomethyl propanol, Aloe Barbadensis leaf Juice, Denatonium benzoate, Fragrance, Glycerin, Maltodextrin, Propylene Glycol, Tocopheryl Acetate, Water.

Package Label - Principal Display Panel

1000 mL NDC: 42509-036-01